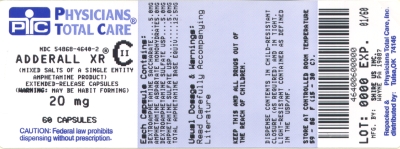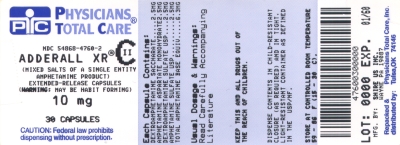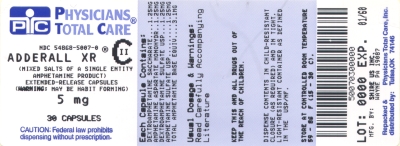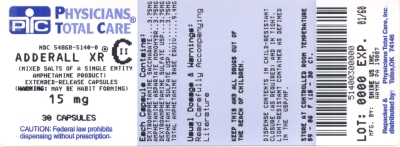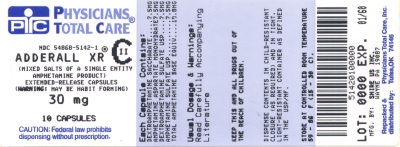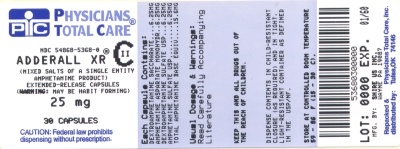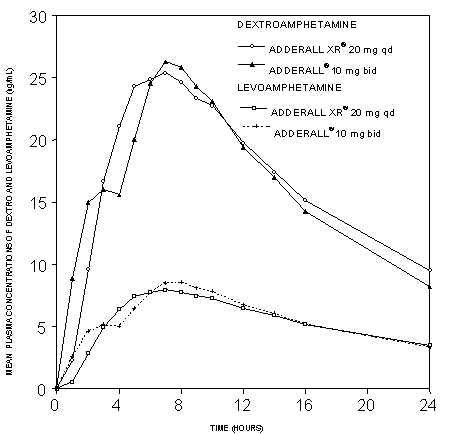 DRUG LABEL: Adderall
NDC: 54868-5007 | Form: CAPSULE, EXTENDED RELEASE
Manufacturer: Physicians Total Care, Inc.
Category: prescription | Type: HUMAN PRESCRIPTION DRUG LABEL
Date: 20120925
DEA Schedule: CII

ACTIVE INGREDIENTS: DEXTROAMPHETAMINE SULFATE 1.25 mg/1 1; DEXTROAMPHETAMINE SACCHARATE 1.25 mg/1 1; AMPHETAMINE ASPARTATE 1.25 mg/1 1; AMPHETAMINE SULFATE 1.25 mg/1 1
INACTIVE INGREDIENTS: GELATIN; HYPROMELLOSES; METHACRYLIC ACID - METHYL METHACRYLATE COPOLYMER (1:1); SUCROSE; TALC; TRIETHYL CITRATE; FD&C BLUE NO. 2

HIGHLIGHTS OF PRESCRIBING INFORMATION

These highlights do not include all the information needed to use ADDERALL XR safely and effectively. See full prescribing information for ADDERALL XR.
ADDERALL XR® (mixed salts of a single-entity amphetamine product) dextroamphetamine sulfate, dextroamphetamine saccharate, amphetamine aspartate monohydrate, amphetamine sulfate capsules, CII
Initial U.S. Approval: 2001

WARNING: POTENTIAL FOR ABUSE

See full prescribing information for complete boxed warning

- Amphetamines have a high potential for abuse; prolonged administration may lead to dependence. (9)
- Misuse of amphetamines may cause sudden death and serious cardiovascular adverse reactions.

1 INDICATIONS AND USAGE

ADDERALL XR, a CNS stimulant, is indicated for the treatment of attention deficit hyperactivity disorder (ADHD). (1)

- Children (ages 6-12): Efficacy was established in one 3-week outpatient, controlled trial and one analogue classroom, controlled trial in children with ADHD. (14)
- Adolescents (ages 13-17): Efficacy was established in one 4-week controlled trial in adolescents with ADHD. (14)
- Adults: Efficacy was established in one 4-week controlled trial in adults with ADHD. (14)

2 DOSAGE and ADMINISTRATION

- Pediatric patients (ages 6-17): 10 mg once daily in the morning. The maximum dose for children 6-12 is 30 mg once daily. (2.1, 2.2, 2.3)
- Adults: 20 mg once daily in the morning. (2.4)

3 DOSAGE FORM AND STRENGTHS

- Capsules: 5 mg, 10 mg, 15 mg, 20 mg, 25 mg, 30 mg (3)

4 CONTRAINDICATIONS

- Advanced arteriosclerosis (4)
- Symptomatic cardiovascular disease (4)
- Moderate to severe hypertension (4)
- Hyperthyroidism (4)
- Known hypersensitivity or idiosyncrasy to the sympathomimetic amines (4)
- Glaucoma (4)
- Agitated states (4)
- History of drug abuse (4)
- During or within 14 days following the administration of monoamine oxidase inhibitors (MAOI) (4, 7.1)

5 WARNINGS and PRECAUTIONS

- Serious Cardiovascular Events: Sudden death has been reported with usual doses of CNS stimulants in children and adolescents with structural cardiac abnormalities or other serious heart problems; sudden death, stroke, and myocardial infarction have been reported in adults taking CNS stimulants at usual doses. Stimulant drugs should not be used in patients with known structural cardiac abnormalities, cardiomyopathy, serious heart rhythm abnormalities, coronary artery disease, or other serious heart problems. (5.1)
- Increase in Blood Pressure: Monitor blood pressure and pulse at appropriate intervals. Use with caution in patients for whom blood pressure increases may be problematic. (5.1)
- Psychiatric Adverse Events: Stimulants may cause treatment-emergent psychotic or manic symptoms in patients with no prior history, or exacerbation of symptoms in patients with pre-existing psychosis. Evaluate for bipolar disorder prior to stimulant use. Monitor for aggressive behavior. (5.2)
- Long-term Suppression of Growth: Monitor height and weight at appropriate intervals. (5.3)
- Seizures: May lower the convulsive threshold. Discontinue in the presence of seizures. (5.4)
- Visual Disturbance: Difficulties with accommodation and blurring of vision have been reported with stimulant treatment. (5.5)
- Tics: May exacerbate tics. Evaluate for tics and Tourette's syndrome prior to stimulant administration. (5.6)

6 ADVERSE REACTIONS

- Children (ages 6 to 12): Most common adverse reactions (≥5% and with a higher incidence than on placebo) were loss of appetite, insomnia, abdominal pain, emotional lability, vomiting, nervousness, nausea and fever. (6.1)
- Adolescents (ages 13 to 17): Most common adverse reactions (≥5% and with a higher incidence than on placebo) were loss of appetite, insomnia, abdominal pain, weight loss, and nervousness. (6.1)
- Adults: Most common adverse reactions ≥5% and with a higher incidence than on placebo were dry mouth, loss of appetite, insomnia, headache, weight loss, nausea, anxiety, agitation, dizziness, tachycardia, diarrhea, asthenia, and urinary tract infections. (6.1)

To report SUSPECTED ADVERSE REACTIONS, contact Shire US Inc. at 1-800-828-2088 or FDA at 1-800-FDA-1088 or www.fda.gov/medwatch

7 DRUG INTERACTIONS

- MAOI antidepressants are contraindicated; MAOIs potentiate the effects of amphetamine. Do not administer ADDERALL XR during or within 14 days after use of MAOI. (4; 7.1)
- Alkalinizing agents (GI antacids and urinary): These agents increase blood levels of amphetamine. (7.1)
- Acidifying agents (GI and urinary): These agents reduce blood levels of amphetamine. (7.2)
- Adrenergic blockers, antihistamines, antihypertensives, phenobarbital, phenytoin, veratrum alkaloids, and ethosuximide: Effects may be reduced by amphetamines. (7.3)
- Tricyclic antidepressants, norepinephrine, and meperidine: Effects may be potentiated by amphetamines. (7.4)

8 USE IN SPECIFIC POPULATIONS

- Pregnancy: Use only if the potential benefit justifies the potential risk to the fetus. Based on animal data, may cause fetal harm. (8.1)
- Nursing Mothers: should refrain from breastfeeding. (8.3)
- Pediatric Use: has not been studied in children under 6 years of age. (8.4)
- Geriatric Use: has not been studied in geriatric patients. (8.5)

FULL PRESCRIBING INFORMATION

WARNING: POTENTIAL FOR ABUSE

Amphetamines have a high potential for abuse . Administration of amphetamines for prolonged periods of time may lead to drug dependence. Pay particular attention to the possibility of subjects obtaining amphetamines for non-therapeutic use or distribution to others and the drugs should be prescribed or dispensed sparingly [see DRUG ABUSE AND DEPENDENCE (9)].

Misuse of amphetamine may cause sudden death and serious cardiovascular adverse reactions.

1 INDICATIONS AND USAGE

1.1 Attention Deficit Hyperactivity Disorder

ADDERALL XR® is indicated for the treatment of attention deficit hyperactivity disorder (ADHD).

The efficacy of ADDERALL XR in the treatment of ADHD was established on the basis of two controlled trials in children aged 6 to 12, one controlled trial in adolescents aged 13 to 17, and one controlled trial in adults who met DSM-IV® criteria for ADHD [see CLINICAL STUDIES (14)].

A diagnosis of ADHD (DSM-IV®) implies the presence of hyperactive-impulsive or inattentive symptoms that caused impairment and were present before age 7 years. The symptoms must cause clinically significant impairment, e.g., in social, academic, or occupational functioning, and be present in two or more settings, e.g., school (or work) and at home. The symptoms must not be better accounted for by another mental disorder. For the Inattentive Type, at least six of the following symptoms must have persisted for at least 6 months: lack of attention to details/careless mistakes; lack of sustained attention; poor listener; failure to follow through on tasks; poor organization; avoids tasks requiring sustained mental effort; loses things; easily distracted; forgetful. For the Hyperactive-Impulsive Type, at least six of the following symptoms must have persisted for at least 6 months: fidgeting/squirming; leaving seat; inappropriate running/climbing; difficulty with quiet activities; "on the go;" excessive talking; blurting answers; can't wait turn; intrusive. The Combined Type requires both inattentive and hyperactive-impulsive criteria to be met.

Special Diagnostic Considerations

Specific etiology of this syndrome is unknown, and there is no single diagnostic test. Adequate diagnosis requires the use not only of medical but of special psychological, educational, and social resources. Learning may or may not be impaired. The diagnosis must be based upon a complete history and evaluation of the patient and not solely on the presence of the required number of DSM-IV® characteristics.

Need for Comprehensive Treatment Program

ADDERALL XR is indicated as an integral part of a total treatment program for ADHD that may include other measures (psychological, educational, social) for patients with this syndrome. Drug treatment may not be indicated for all patients with this syndrome. Stimulants are not intended for use in the patient who exhibits symptoms secondary to environmental factors and/or other primary psychiatric disorders, including psychosis. Appropriate educational placement is essential and psychosocial intervention is often helpful. When remedial measures alone are insufficient, the decision to prescribe stimulant medication will depend upon the physician's assessment of the chronicity and severity of the child's symptoms.

Long-Term Use

The effectiveness of ADDERALL XR for long-term use, i.e., for more than 3 weeks in children and 4 weeks in adolescents and adults, has not been systematically evaluated in controlled trials. Therefore, the physician who elects to use ADDERALL XR for extended periods should periodically re-evaluate the long-term usefulness of the drug for the individual patient.

2 DOSAGE and ADMINISTRATION

2.1 Dosing Considerations for all Patients

Individualize the dosage according to the therapeutic needs and response of the patient. Administer ADDERALL XR at the lowest effective dosage.

Based on bioequivalence data, patients taking divided doses of immediate-release ADDERALL, (for example, twice daily), may be switched to ADDERALL XR at the same total daily dose taken once daily. Titrate at weekly intervals to appropriate efficacy and tolerability as indicated.

ADDERALL XR capsules may be taken whole, or the capsule may be opened and the entire contents sprinkled on applesauce. If the patient is using the sprinkle administration method, the sprinkled applesauce should be consumed immediately; it should not be stored. Patients should take the applesauce with sprinkled beads in its entirety without chewing. The dose of a single capsule should not be divided. The contents of the entire capsule should be taken, and patients should not take anything less than one capsule per day.

ADDERALL XR may be taken with or without food.

ADDERALL XR should be given upon awakening. Afternoon doses should be avoided because of the potential for insomnia.

Where possible, ADDERALL XR therapy should be interrupted occasionally to determine if there is a recurrence of behavioral symptoms sufficient to require continued therapy.

2.2 Children

In children with ADHD who are 6-12 years of age and are either starting treatment for the first time or switching from another medication, start with 10 mg once daily in the morning; daily dosage may be adjusted in increments of 5 mg or 10 mg at weekly intervals. When in the judgment of the clinician a lower initial dose is appropriate, patients may begin treatment with 5 mg once daily in the morning. The maximum recommended dose for children is 30 mg/day; doses greater than 30 mg/day of ADDERALL XR have not been studied in children. ADDERALL XR has not been studied in children under 6 years of age.

2.3 Adolescents

The recommended starting dose for adolescents with ADHD who are 13-17 years of age and are either starting treatment for the first time or switching from another medication is 10 mg/day. The dose may be increased to 20 mg/day after one week if ADHD symptoms are not adequately controlled.

2.4 Adults

In adults with ADHD who are either starting treatment for the first time or switching from another medication, the recommended dose is 20 mg/day.

3 DOSAGE FORM AND STRENGTHS

ADDERALL XR 5 mg capsules: Clear/blue (imprinted ADDERALL XR 5 mg)

ADDERALL XR 10 mg capsules: Blue/blue (imprinted ADDERALL XR 10 mg)

ADDERALL XR 15 mg capsules: Blue/white (imprinted ADDERALL XR 15 mg)

ADDERALL XR 20 mg capsules: Orange/orange (imprinted ADDERALL XR 20 mg)

ADDERALL XR 25 mg capsules: Orange/white (imprinted ADDERALL XR 25 mg)

ADDERALL XR 30 mg capsules: Natural/orange (imprinted ADDERALL XR 30 mg)

4 CONTRAINDICATIONS

ADDERALL XR administration is contraindicated in patients with the following conditions:

- Advanced arteriosclerosis
- Symptomatic cardiovascular disease
- Moderate to severe hypertension
- Hyperthyroidism
- Known hypersensitivity or idiosyncrasy to the sympathomimetic amines (e.g., anaphylaxis, angioedema, serious skin rashes) [see ADVERSE REACTIONS (6.2)]
- Glaucoma
- Agitated states
- History of drug abuse
- During or within 14 days following the administration of monoamine oxidase inhibitors (hypertensive crises may result) [see DRUG INTERACTIONS (7.1)]

5 WARNINGS and PRECAUTIONS

5.1 Serious Cardiovascular Events

Sudden Death and Pre-existing Structural Cardiac Abnormalities or Other Serious Heart Problems

Children and Adolescents

Sudden death has been reported in association with CNS stimulant treatment at usual doses in children and adolescents with structural cardiac abnormalities or other serious heart problems. Although some serious heart problems alone carry an increased risk of sudden death, stimulant products generally should not be used in children or adolescents with known serious structural cardiac abnormalities, cardiomyopathy, serious heart rhythm abnormalities, or other serious cardiac problems that may place them at increased vulnerability to the sympathomimetic effects of a stimulant drug [see CONTRAINDICATIONS (4)].

Adults

Sudden deaths, stroke, and myocardial infarction have been reported in adults taking stimulant drugs at usual doses for ADHD. Although the role of stimulants in these adult cases is also unknown, adults have a greater likelihood than children of having serious structural cardiac abnormalities, cardiomyopathy, serious heart rhythm abnormalities, coronary artery disease, or other serious cardiac problems. Adults with such abnormalities should also generally not be treated with stimulant drugs [see CONTRAINDICATIONS (4)].

Hypertension and Other Cardiovascular Conditions

Stimulant medications cause a modest increase in average blood pressure (about 2-4 mmHg) and average heart rate (about 3-6 bpm), and individuals may have larger increases. While the mean changes alone would not be expected to have short-term consequences, all patients should be monitored for larger changes in heart rate and blood pressure. Caution is indicated in treating patients whose underlying medical conditions might be compromised by increases in blood pressure or heart rate, e.g., those with pre-existing hypertension, heart failure, recent myocardial infarction, or ventricular arrhythmia [see CONTRAINDICATIONS (4) and ADVERSE REACTIONS (6)].

Assessing Cardiovascular Status in Patients being Treated with Stimulant Medications

Children, adolescents, or adults who are being considered for treatment with stimulant medications should have a careful history (including assessment for a family history of sudden death or ventricular arrhythmia) and physical exam to assess for the presence of cardiac disease, and should receive further cardiac evaluation if findings suggest such disease (e.g. electrocardiogram and echocardiogram). Patients who develop symptoms such as exertional chest pain, unexplained syncope, or other symptoms suggestive of cardiac disease during stimulant treatment should undergo a prompt cardiac evaluation.

5.2 Psychiatric Adverse Events

Pre-Existing Psychosis

Administration of stimulants may exacerbate symptoms of behavior disturbance and thought disorder in patients with pre-existing psychotic disorder.

Bipolar Illness

Particular care should be taken in using stimulants to treat ADHD patients with comorbid bipolar disorder because of concern for possible induction of mixed/manic episode in such patients. Prior to initiating treatment with a stimulant, patients with comorbid depressive symptoms should be adequately screened to determine if they are at risk for bipolar disorder; such screening should include a detailed psychiatric history, including a family history of suicide, bipolar disorder, and depression.

Emergence of New Psychotic or Manic Symptoms

Treatment-emergent psychotic or manic symptoms, e.g., hallucinations, delusional thinking, or mania in children and adolescents without prior history of psychotic illness or mania can be caused by stimulants at usual doses. If such symptoms occur, consideration should be given to a possible causal role of the stimulant, and discontinuation of treatment may be appropriate. In a pooled analysis of multiple short-term, placebo-controlled studies, such symptoms occurred in about 0.1% (4 patients with events out of 3482 exposed to methylphenidate or amphetamine for several weeks at usual doses) of stimulant-treated patients compared to 0 in placebo-treated patients.

Aggression

Aggressive behavior or hostility is often observed in children and adolescents with ADHD, and has been reported in clinical trials and the postmarketing experience of some medications indicated for the treatment of ADHD. Although there is no systematic evidence that stimulants cause aggressive behavior or hostility, patients beginning treatment for ADHD should be monitored for the appearance of or worsening of aggressive behavior or hostility.

5.3 Long-Term Suppression of Growth

Monitor growth in children during treatment with stimulants. Patients who are not growing or gaining weight as expected may need to have their treatment interrupted.

Careful follow-up of weight and height in children ages 7 to 10 years who were randomized to either methylphenidate or non-medication treatment groups over 14 months, as well as in naturalistic subgroups of newly methylphenidate-treated and non-medication treated children over 36 months (to the ages of 10 to 13 years), suggests that consistently medicated children (i.e., treatment for 7 days per week throughout the year) have a temporary slowing in growth rate (on average, a total of about 2 cm less growth in height and 2.7 kg less growth in weight over 3 years), without evidence of growth rebound during this period of development.

In a controlled trial of ADDERALL XR in adolescents, mean weight change from baseline within the initial 4 weeks of therapy was -1.1 lbs. and -2.8 lbs., respectively, for patients receiving 10 mg and 20 mg ADDERALL XR. Higher doses were associated with greater weight loss within the initial 4 weeks of treatment. Chronic use of amphetamines can be expected to cause a similar suppression of growth.

5.4 Seizures

There is some clinical evidence that stimulants may lower the convulsive threshold in patients with prior history of seizures, in patients with prior EEG abnormalities in the absence of seizures, and very rarely, in patients without a history of seizures and no prior EEG evidence of seizures. In the presence of seizures, ADDERALL XR should be discontinued.

5.5 Visual Disturbance

Difficulties with accommodation and blurring of vision have been reported with stimulant treatment.

5.6 Tics

Amphetamines have been reported to exacerbate motor and phonic tics and Tourette's syndrome. Therefore, clinical evaluation for tics and Tourette's syndrome in patients and their families should precede use of stimulant medications.

5.7 Prescribing and Dispensing

The least amount of amphetamine feasible should be prescribed or dispensed at one time in order to minimize the possibility of overdosage. ADDERALL XR should be used with caution in patients who use other sympathomimetic drugs.

6 ADVERSE REACTIONS

Because clinical trials are conducted under widely varying conditions, adverse reaction rates observed in the clinical trials of a drug cannot be directly compared to rates in the clinical trials of another drug and may not reflect the rates observed in clinical practice.

6.1 Clinical Studies Experience

The premarketing development program for ADDERALL XR included exposures in a total of 1315 participants in clinical trials (635 pediatric patients, 350 adolescent patients, 248 adult patients, and 82 healthy adult subjects). Of these, 635 patients (ages 6 to 12) were evaluated in two controlled clinical studies, one open-label clinical study, and two single-dose clinical pharmacology studies (N= 40). Safety data on all patients are included in the discussion that follows. Adverse reactions were assessed by collecting adverse reactions, results of physical examinations, vital signs, weights, laboratory analyses, and ECGs.

Adverse reactions during exposure were obtained primarily by general inquiry and recorded by clinical investigators using terminology of their own choosing. Consequently, it is not possible to provide a meaningful estimate of the proportion of individuals experiencing adverse reactions without first grouping similar types of reactions into a smaller number of standardized event categories. In the tables and listings that follow, COSTART terminology has been used to classify reported adverse reactions.

The stated frequencies of adverse reactions represent the proportion of individuals who experienced, at least once, a treatment-emergent adverse event of the type listed.

Adverse Reactions Leading to Discontinuation of Treatment

In two placebo-controlled studies of up to 5 weeks duration among children with ADHD, 2.4% (10/425) of ADDERALL XR-treated patients discontinued due to adverse reactions (including 3 patients with loss of appetite, one of whom also reported insomnia) compared to 2.7% (7/259) receiving placebo.

The most frequent adverse reactions leading to discontinuation of ADDERALL XR in controlled and uncontrolled, multiple-dose clinical trials of children (N=595) were anorexia (loss of appetite) (2.9%), insomnia (1.5%), weight loss (1.2%), emotional lability (1%), and depression (0.7%). Over half of these patients were exposed to ADDERALL XR for 12 months or more.

In a separate placebo-controlled 4-week study in adolescents with ADHD, five patients (2.1%) discontinued treatment due to adverse events among ADDERALL XR-treated patients (N=233) compared to none who received placebo (N=54). The most frequent adverse event leading to discontinuation and considered to be drug-related (i.e. leading to discontinuation in at least 1% of ADDERALL XR-treated patients and at a rate at least twice that of placebo) was insomnia (1.3%, n=3).

In one placebo-controlled 4-week study among adults with ADHD with doses 20 mg to 60 mg, 23 patients (12.0%) discontinued treatment due to adverse events among ADDERALL XR-treated patients (N=191) compared to one patient (1.6%) who received placebo (N=64). The most frequent adverse events leading to discontinuation and considered to be drug-related (i.e. leading to discontinuation in at least 1% of ADDERALL XR-treated patients and at a rate at least twice that of placebo) were insomnia (5.2%, n=10), anxiety (2.1%, n=4), nervousness (1.6%, n=3), dry mouth (1.6%, n=3), anorexia (1.6%, n=3), tachycardia (1.6%, n=3), headache (1.6%, n=3), and asthenia (1.0%, n=2).

Adverse Reactions Occurring in Controlled Trials

Adverse reactions reported in a 3-week clinical trial of children and a 4-week clinical trial in adolescents and adults, respectively, treated with ADDERALL XR or placebo are presented in the tables below.

Table 1 Adverse Reactions Reported by 2% or More of Children (6-12 Years Old) Receiving ADDERALL XR with Higher Incidence Than on Placebo in a 584-Patient Clinical Study
Body System | Preferred Term | ADDERALL XR (n=374) | Placebo (n=210)
General | Abdominal Pain (stomachache) Fever Infection Accidental Injury Asthenia (fatigue) | 14% 5% 4% 3% 2% | 10% 2% 2% 2% 0%
Digestive System | Loss of Appetite Vomiting Nausea Dyspepsia | 22% 7% 5% 2% | 2% 4% 3% 1%
Nervous System | Insomnia Emotional Lability Nervousness Dizziness | 17% 9% 6% 2% | 2% 2% 2% 0%
Metabolic/Nutritional | Weight Loss | 4% | 0%

Table 2 Adverse Reactions Reported by 5% or More of Adolescents (13-17 Years Old) Weighing ≤ 75 kg/165 lbs Receiving ADDERALL XR with Higher Incidence Than Placebo in a 287 Patient Clinical Forced Weekly-Dose Titration Study*
Body System | Preferred Term | ADDERALL XR (n=233) | Placebo (n=54)
General | Abdominal Pain (stomachache) | 11% | 2%
Digestive System | Loss of Appetite b | 36% | 2%
Nervous System | Insomnia b Nervousness | 12% 6% | 4% 6%a
Metabolic/Nutritional | Weight Loss b | 9% | 0%
*Included doses up to 40 mg
a Appears the same due to rounding
b Dose-related adverse reactions
Note: The following reactions did not meet the criterion for inclusion in Table 2 but were reported by 2% to 4% of adolescent patients receiving ADDERALL XR with a higher incidence than patients receiving placebo in this study: accidental injury, asthenia (fatigue), dry mouth, dyspepsia, emotional lability, nausea, somnolence, and vomiting.

Table 3 Adverse Reactions Reported by 5% or More of Adults Receiving ADDERALL XR with Higher Incidence Than on Placebo in a 255 Patient Clinical Forced Weekly-Dose Titration Study*
Body System | Preferred Term | ADDERALL XR (n=191) | Placebo (n=64)
General | Headache Asthenia | 26% 6% | 13% 5%
Digestive System | Dry Mouth Loss of Appetite Nausea Diarrhea | 35% 33% 8% 6% | 5% 3% 3% 0%
Nervous System | Insomnia Agitation Anxiety Dizziness | 27% 8% 8% 7% | 13% 5% 5% 0%
Cardiovascular System | Tachycardia | 6% | 3%
Metabolic/Nutritional | Weight Loss | 11% | 0%
Urogenital System | Urinary Tract Infection | 5% | 0%
*Included doses up to 60 mg.
Note: The following reactions did not meet the criterion for inclusion in Table 3 but were reported by 2% to 4% of adult patients receiving ADDERALL XR with a higher incidence than patients receiving placebo in this study: infection, photosensitivity reaction, constipation, tooth disorder (e.g., teeth clenching, tooth infection), emotional lability, libido decreased, somnolence, speech disorder (e.g., stuttering, excessive speech), palpitation, twitching, dyspnea, sweating, dysmenorrhea, and impotence.

Hypertension [see WARNINGS AND PRECAUTIONS (5.1)]

In a controlled 4-week outpatient clinical study of adolescents with ADHD, isolated systolic blood pressure elevations ≥15 mmHg were observed in 7/64 (11%) placebo-treated patients and 7/100 (7%) patients receiving ADDERALL XR 10 or 20 mg. Isolated elevations in diastolic blood pressure ≥ 8 mmHg were observed in 16/64 (25%) placebo-treated patients and 22/100 (22%) ADDERALL XR-treated patients. Similar results were observed at higher doses.

In a single-dose pharmacokinetic study in 23 adolescents with ADHD, isolated increases in systolic blood pressure (above the upper 95% CI for age, gender, and stature) were observed in 2/17 (12%) and 8/23 (35%), subjects administered 10 mg and 20 mg ADDERALL XR, respectively. Higher single doses were associated with a greater increase in systolic blood pressure. All increases were transient, appeared maximal at 2 to 4 hours post dose and not associated with symptoms.

6.2 Adverse Reactions Associated with the Use of Amphetamine, ADDERALL XR, or ADDERALL

The following adverse reactions have been associated with the use of amphetamine, ADDERALL XR, or ADDERALL:

Cardiovascular

Palpitations. There have been isolated reports of cardiomyopathy associated with chronic amphetamine use.

Central Nervous System

Psychotic episodes at recommended doses, overstimulation, restlessness, irritability, euphoria, dyskinesia, dysphoria, depression, tremor, tics, aggression, anger, logorrhea, dermatillomania.

Eye Disorders

Vision blurred, mydriasis.

Gastrointestinal

Unpleasant taste, constipation, other gastrointestinal disturbances.

Allergic

Urticaria, rash, hypersensitivity reactions including angioedema and anaphylaxis. Serious skin rashes, including Stevens-Johnson Syndrome and toxic epidermal necrolysis have been reported.

Endocrine

Impotence, changes in libido.

Skin

Alopecia.

7 DRUG INTERACTIONS

7.1 Agents that Increase Blood Levels of Amphetamines

MAO Inhibitors

MAOI antidepressants slow amphetamine metabolism. This slowing potentiates amphetamines, increasing their effect on the release of norepinephrine and other monoamines from adrenergic nerve endings; this can cause headaches and other signs of hypertensive crisis. A variety of toxic neurological effects and malignant hyperpyrexia can occur, sometimes with fatal results. Do not administer ADDERALL XR during or within 14 days following the administration of monoamine oxidase inhibitors [see CONTRAINDICATIONS (4)].

Alkalinizing Agents

Gastrointestinal alkalinizing agents (e.g., sodium bicarbonate) increase absorption of amphetamines. Co-administration of ADDERALL XR and gastrointestinal alkalinizing agents, such as antacids, should be avoided. Urinary alkalinizing agents (acetazolamide, some thiazides) increase the concentration of the non-ionized species of the amphetamine molecule, thereby decreasing urinary excretion. Both groups of agents increase blood levels and therefore potentiate the actions of amphetamines.

7.2 Agents that Lower Blood Levels of Amphetamines

Acidifying Agents

Gastrointestinal acidifying agents (e.g., guanethidine, reserpine, glutamic acid HCl, ascorbic acid) lower absorption of amphetamines. Urinary acidifying agents (e.g., ammonium chloride, sodium acid phosphate, methenamine salts) increase the concentration of the ionized species of the amphetamine molecule, thereby increasing urinary excretion. Both groups of agents lower blood levels and efficacy of amphetamines.

7.3 Agents whose Effects May be Reduced by Amphetamines

Adrenergic Blockers

Amphetamines may reduce the cardiovascular effects of adrenergic blockers.

Antihistamines

Amphetamines may counteract the sedative effect of antihistamines.

Antihypertensives

Amphetamines may antagonize the hypotensive effects of antihypertensives.

Veratrum alkaloids

Amphetamines inhibit the hypotensive effect of veratrum alkaloids.

Phenobarbital

Amphetamines may delay intestinal absorption of phenobarbital.

Phenytoin

Amphetamines may delay intestinal absorption of phenytoin.

Ethosuximide

Amphetamines may delay intestinal absorption of ethosuximide.

7.4 Agents whose Effects May be Potentiated by Amphetamines

Antidepressants, Tricyclic

Amphetamines may enhance the activity of tricyclic antidepressants or sympathomimetic agents; d-amphetamine with desipramine or protriptyline and possibly other tricyclics cause striking and sustained increases in the concentration of d-amphetamine in the brain; cardiovascular effects can be potentiated.

Meperidine

Amphetamines potentiate the analgesic effect of meperidine.

Norepinephrine

Amphetamines may enhance the adrenergic effect of norepinephrine.

7.5 Agents that May Reduce the Effects of Amphetamines

Chlorpromazine

Chlorpromazine blocks dopamine and norepinephrine receptors, thus inhibiting the central stimulant effects of amphetamines.

Haloperidol

Haloperidol blocks dopamine receptors, thus inhibiting the central stimulant effects of amphetamines.

Lithium Carbonate

The anorectic and stimulatory effects of amphetamines may be inhibited by lithium carbonate.

7.6 Agents that May Potentiate the Effects of Amphetamines

Norepinephrine

Norepinephrine may enhance the adrenergic effect of amphetamine.

Propoxyphene Overdosage

In cases of propoxyphene overdosage, amphetamine CNS stimulation is potentiated and fatal convulsions can occur.

7.7 Proton Pump Inhibitors

PPIs act on proton pumps by blocking acid production, thereby reducing gastric acidity. When ADDERALL XR (20 mg single-dose) was administered concomitantly with the proton pump inhibitor, omeprazole (40 mg once daily for 14 days), the median Tmax of d-amphetamine was decreased by 1.25 hours (from 4 to 2.75 hours), and the median Tmax of l-amphetamine was decreased by 2.5 hours (from 5.5 to 3 hours), compared to ADDERALL XR administered alone. The AUC and Cmax of each moiety were unaffected. Therefore, co-administration of ADDERALL XR and proton pump inhibitors should be monitored for changes in clinical effect.

7.8 Drug/Laboratory Test Interactions

Amphetamines can cause a significant elevation in plasma corticosteroid levels. This increase is greatest in the evening. Amphetamines may interfere with urinary steroid determinations.

8 USE IN SPECIFIC POPULATIONS

8.1 Pregnancy

Teratogenic Effects

Pregnancy Category C.

Amphetamine, in the enantiomer ratio present in ADDERALL XR (d- to l- ratio of 3:1), had no apparent effects on embryofetal morphological development or survival when orally administered to pregnant rats and rabbits throughout the period of organogenesis at doses of up to 6 and 16 mg/kg/day, respectively. These doses are approximately 2 and 12 times, respectively, the maximum recommended human dose (MRHD) for adolescents of 20 mg/day, on a mg/m^2 body surface area basis. Fetal malformations and death have been reported in mice following parenteral administration of d-amphetamine doses of 50 mg/kg/day (approximately 10 times the MRHD for adolescents on a mg/m^2 basis) or greater to pregnant animals. Administration of these doses was also associated with severe maternal toxicity.

A study was conducted in which pregnant rats received daily oral doses of amphetamine (d- to l- enantiomer ratio of 3:1, the same as in ADDERALL XR) of 2, 6, and 10 mg/kg from gestation day 6 to lactation day 20. These doses are approximately 0.8, 2, and 4 times the MRHD for adolescents of 20 mg/day, on a mg/m^2 basis. All doses caused hyperactivity and decreased weight gain in the dams. A decrease in pup survival was seen at all doses. A decrease in pup bodyweight was seen at 6 and 10 mg/kg which correlated with delays in developmental landmarks. Increased pup locomotor activity was seen at 10 mg/kg on day 22 postpartum but not at 5 weeks postweaning. When pups were tested for reproductive performance at maturation, gestational weight gain, number of implantations, and number of delivered pups were decreased in the group whose mothers had been given 10 mg/kg.

A number of studies in rodents indicate that prenatal or early postnatal exposure to amphetamine (d- or d, l-), at doses similar to those used clinically, can result in long-term neurochemical and behavioral alterations. Reported behavioral effects include learning and memory deficits, altered locomotor activity, and changes in sexual function.

There are no adequate and well-controlled studies in pregnant women. There has been one report of severe congenital bony deformity, tracheo-esophageal fistula, and anal atresia (vater association) in a baby born to a woman who took dextroamphetamine sulfate with lovastatin during the first trimester of pregnancy. Amphetamines should be used during pregnancy only if the potential benefit justifies the potential risk to the fetus.

Nonteratogenic Effects

Infants born to mothers dependent on amphetamines have an increased risk of premature delivery and low birth weight. Also, these infants may experience symptoms of withdrawal as demonstrated by dysphoria, including agitation, and significant lassitude.

8.2 Labor and Delivery

The effects of ADDERALL XR on labor and delivery in humans is unknown.

8.3 Nursing Mothers

Amphetamines are excreted in human milk. Mothers taking amphetamines should be advised to refrain from nursing.

8.4 Pediatric Use

ADDERALL XR is indicated for use in children 6 years of age and older.

The safety and efficacy of ADDERALL XR in children under 6 years of age have not been studied. Long-term effects of amphetamines in children have not been well established.

In a juvenile developmental study, rats received daily oral doses of amphetamine (d to l enantiomer ratio of 3:1, the same as in ADDERALL XR) of 2, 6, or 20 mg/kg on days 7-13 of age; from day 14 to approximately day 60 of age these doses were given b.i.d. for total daily doses of 4, 12, or 40 mg/kg. The latter doses are approximately 0.6, 2, and 6 times the maximum recommended human dose for children of 30 mg/day, on a mg/m^2 basis. Post dosing hyperactivity was seen at all doses; motor activity measured prior to the daily dose was decreased during the dosing period but the decreased motor activity was largely absent after an 18 day drug-free recovery period. Performance in the Morris water maze test for learning and memory was impaired at the 40 mg/kg dose, and sporadically at the lower doses, when measured prior to the daily dose during the treatment period; no recovery was seen after a 19 day drug-free period. A delay in the developmental milestones of vaginal opening and preputial separation was seen at 40 mg/kg but there was no effect on fertility.

8.5 Geriatric Use

ADDERALL XR has not been studied in the geriatric population.

9 DRUG ABUSE AND DEPENDENCE

9.1 Controlled Substance

ADDERALL XR is a Schedule II controlled substance.

9.2 Abuse and Dependence

Amphetamines have been extensively abused. Tolerance, extreme psychological dependence, and severe social disability have occurred. There are reports of patients who have increased the dosage to levels many times higher than recommended. Abrupt cessation following prolonged high dosage administration results in extreme fatigue and mental depression; changes are also noted on the sleep EEG. Manifestations of chronic intoxication with amphetamines may include severe dermatoses, marked insomnia, irritability, hyperactivity, and personality changes. The most severe manifestation of chronic intoxication is psychosis, often clinically indistinguishable from schizophrenia.

10 OVERDOSAGE

Individual patient response to amphetamines varies widely. Toxic symptoms may occur idiosyncratically at low doses.

Symptoms

Manifestations of acute overdosage with amphetamines include restlessness, tremor, hyperreflexia, rapid respiration, confusion, assaultiveness, hallucinations, panic states, hyperpyrexia and rhabdomyolysis. Fatigue and depression usually follow the central nervous system stimulation. Cardiovascular effects include arrhythmias, hypertension or hypotension and circulatory collapse. Gastrointestinal symptoms include nausea, vomiting, diarrhea, and abdominal cramps. Fatal poisoning is usually preceded by convulsions and coma.

Treatment

Consult with a Certified Poison Control Center for up to date guidance and advice.

The prolonged release of mixed amphetamine salts from ADDERALL XR should be considered when treating patients with overdose.

11 DESCRIPTION

ADDERALL XR is a once daily extended-release, single-entity amphetamine product. ADDERALL XR combines the neutral sulfate salts of dextroamphetamine and amphetamine, with the dextro isomer of amphetamine saccharate and d,l-amphetamine aspartate monohydrate. The ADDERALL XR capsule contains two types of drug-containing beads designed to give a double-pulsed delivery of amphetamines, which prolongs the release of amphetamine from ADDERALL XR compared to the conventional ADDERALL (immediate-release) tablet formulation.

EACH CAPSULE CONTAINS: | 5 mg | 10 mg | 15 mg | 20 mg | 25 mg | 30 mg
Dextroamphetamine Saccharate | 1.25 mg | 2.5 mg | 3.75 mg | 5.0 mg | 6.25 mg | 7.5 mg
Amphetamine Aspartate Monohydrate | 1.25 mg | 2.5 mg | 3.75 mg | 5.0 mg | 6.25 mg | 7.5 mg
Dextroamphetamine Sulfate USP | 1.25 mg | 2.5 mg | 3.75 mg | 5.0 mg | 6.25 mg | 7.5 mg
Amphetamine Sulfate USP | 1.25 mg | 2.5 mg | 3.75 mg | 5.0 mg | 6.25 mg | 7.5 mg
Total amphetamine base equivalence | 3.1 mg | 6.3 mg | 9.4 mg | 12.5 mg | 15.6 mg | 18.8 mg

Inactive Ingredients and Colors

The inactive ingredients in ADDERALL XR capsules include: gelatin capsules, hydroxypropyl methylcellulose, methacrylic acid copolymer, opadry beige, sugar spheres, talc, and triethyl citrate. Gelatin capsules contain edible inks, kosher gelatin, and titanium dioxide. The 5 mg, 10 mg, and 15 mg capsules also contain FD&C Blue #2. The 20 mg, 25 mg, and 30 mg capsules also contain red iron oxide and yellow iron oxide.

12 CLINICAL PHARMACOLOGY

12.1 Mechanism of Action

Amphetamines are non-catecholamine sympathomimetic amines with CNS stimulant activity. The mode of therapeutic action in ADHD is not known. Amphetamines are thought to block the reuptake of norepinephrine and dopamine into the presynaptic neuron and increase the release of these monoamines into the extraneuronal space.

12.3 Pharmacokinetics

Pharmacokinetic studies of ADDERALL XR have been conducted in healthy adult and pediatric (children aged 6-12 yrs) subjects, and adolescent (13-17 yrs) and children with ADHD. Both ADDERALL (immediate-release) tablets and ADDERALL XR capsules contain d-amphetamine and l-amphetamine salts in the ratio of 3:1. Following administration of ADDERALL (immediate-release), the peak plasma concentrations occurred in about 3 hours for both d-amphetamine and l-amphetamine.

The time to reach maximum plasma concentration (Tmax) for ADDERALL XR is about 7 hours, which is about 4 hours longer compared to ADDERALL(immediate-release). This is consistent with the extended-release nature of the product.

Figure 1 Mean d-amphetamine and l-amphetamine Plasma Concentrations Following Administration of ADDERALL XR 20 mg (8 am) and ADDERALL (immediate-release) 10 mg Twice Daily (8 am and 12 noon) in the Fed State.

A single dose of ADDERALL XR 20 mg capsules provided comparable plasma concentration profiles of both d-amphetamine and l-amphetamine to ADDERALL (immediate-release) 10 mg twice daily administered 4 hours apart.

The mean elimination half-life for d-amphetamine is 10 hours in adults; 11 hours in adolescents aged 13-17 years and weighing less than or equal to 75 kg/165 lbs; and 9 hours in children aged 6 to 12 years. For the l-amphetamine, the mean elimination half-life in adults is 13 hours; 13 to 14 hours in adolescents; and 11 hours in children aged 6 to 12 years. On a mg/kg body weight basis, children have a higher clearance than adolescents or adults (see Special Populations below).

ADDERALL XR demonstrates linear pharmacokinetics over the dose range of 20 to 60 mg in adults and adolescents weighing greater than 75 kg/165 lbs, over the dose range of 10 to 40 mg in adolescents weighing less than or equal to 75 kg/165 lbs, and 5 to 30 mg in children aged 6 to 12 years. There is no unexpected accumulation at steady state in children.

Food does not affect the extent of absorption of d-amphetamine and l-amphetamine, but prolongs Tmax by 2.5 hours (from 5.2 hrs at fasted state to 7.7 hrs after a high-fat meal) for d-amphetamine and 2.1 hours (from 5.6 hrs at fasted state to 7.7 hrs after a high fat meal) for l-amphetamine after administration of ADDERALL XR 30 mg. Opening the capsule and sprinkling the contents on applesauce results in comparable absorption to the intact capsule taken in the fasted state. Equal doses of ADDERALL XR strengths are bioequivalent.

Metabolism and Excretion

Amphetamine is reported to be oxidized at the 4 position of the benzene ring to form 4-hydroxyamphetamine, or on the side chain α or β carbons to form alpha-hydroxy-amphetamine or norephedrine, respectively. Norephedrine and 4-hydroxy-amphetamine are both active and each is subsequently oxidized to form 4-hydroxy-norephedrine. Alpha-hydroxy-amphetamine undergoes deamination to form phenylacetone, which ultimately forms benzoic acid and its glucuronide and the glycine conjugate hippuric acid. Although the enzymes involved in amphetamine metabolism have not been clearly defined, CYP2D6 is known to be involved with formation of 4-hydroxy-amphetamine. Since CYP2D6 is genetically polymorphic, population variations in amphetamine metabolism are a possibility.

Amphetamine is known to inhibit monoamine oxidase, whereas the ability of amphetamine and its metabolites to inhibit various P450 isozymes and other enzymes has not been adequately elucidated. In vitro experiments with human microsomes indicate minor inhibition of CYP2D6 by amphetamine and minor inhibition of CYP1A2, 2D6, and 3A4 by one or more metabolites. However, due to the probability of auto-inhibition and the lack of information on the concentration of these metabolites relative to in vivo concentrations, no predications regarding the potential for amphetamine or its metabolites to inhibit the metabolism of other drugs by CYP isozymes in vivo can be made.

With normal urine pHs, approximately half of an administered dose of amphetamine is recoverable in urine as derivatives of alpha-hydroxy-amphetamine and approximately another 30%-40% of the dose is recoverable in urine as amphetamine itself. Since amphetamine has a pKa of 9.9, urinary recovery of amphetamine is highly dependent on pH and urine flow rates. Alkaline urine pHs result in less ionization and reduced renal elimination, and acidic pHs and high flow rates result in increased renal elimination with clearances greater than glomerular filtration rates, indicating the involvement of active secretion. Urinary recovery of amphetamine has been reported to range from 1% to 75%, depending on urinary pH, with the remaining fraction of the dose hepatically metabolized. Consequently, both hepatic and renal dysfunction have the potential to inhibit the elimination of amphetamine and result in prolonged exposures. In addition, drugs that effect urinary pH are known to alter the elimination of amphetamine, and any decrease in amphetamine's metabolism that might occur due to drug interactions or genetic polymorphisms is more likely to be clinically significant when renal elimination is decreased, [see DRUG INTERACTIONS (7)].

Special Populations

Comparison of the pharmacokinetics of d- and l-amphetamine after oral administration of ADDERALL XR in children (6-12 years) and adolescent (13-17 years) ADHD patients and healthy adult volunteers indicates that body weight is the primary determinant of apparent differences in the pharmacokinetics of d- and l-amphetamine across the age range. Systemic exposure measured by area under the curve to infinity (AUC∞) and maximum plasma concentration (Cmax) decreased with increases in body weight, while oral volume of distribution (VZ/F), oral clearance (CL/F), and elimination half-life (t1/2) increased with increases in body weight.

Pediatric Patients

On a mg/kg weight basis, children eliminated amphetamine faster than adults. The elimination half-life (t1/2) is approximately 1 hour shorter for d-amphetamine and 2 hours shorter for l-amphetamine in children than in adults. However, children had higher systemic exposure to amphetamine (Cmax and AUC) than adults for a given dose of ADDERALL XR, which was attributed to the higher dose administered to children on a mg/kg body weight basis compared to adults. Upon dose normalization on a mg/kg basis, children showed 30% less systemic exposure compared to adults.

Gender

Systemic exposure to amphetamine was 20-30% higher in women (N=20) than in men (N=20) due to the higher dose administered to women on a mg/kg body weight basis. When the exposure parameters (Cmax and AUC) were normalized by dose (mg/kg), these differences diminished. Age and gender had no direct effect on the pharmacokinetics of d- and l-amphetamine.

Race

Formal pharmacokinetic studies for race have not been conducted. However, amphetamine pharmacokinetics appeared to be comparable among Caucasians (N=33), Blacks (N=8) and Hispanics (N=10).

13 NONCLINICAL TOXICOLOGY

13.1 Carcinogenesis, Mutagenesis, Impairment of Fertility

No evidence of carcinogenicity was found in studies in which d,l-amphetamine (enantiomer ratio of 1:1) was administered to mice and rats in the diet for 2 years at doses of up to 30 mg/kg/day in male mice, 19 mg/kg/day in female mice, and 5 mg/kg/day in male and female rats. These doses are approximately 2.4, 1.5, and 0.8 times, respectively, the maximum recommended human dose for children of 30 mg/day, on a mg/m^2 body surface area basis.

Amphetamine, in the enantiomer ratio present in ADDERALL XR (d- to l- ratio of 3:1), was not clastogenic in the mouse bone marrow micronucleus test in vivo and was negative when tested in the E. coli component of the Ames test in vitro. d,l-Amphetamine (1:1 enantiomer ratio) has been reported to produce a positive response in the mouse bone marrow micronucleus test, an equivocal response in the Ames test, and negative responses in the in vitro sister chromatid exchange and chromosomal aberration assays.

Amphetamine, in the enantiomer ratio present in ADDERALL XR (d- to l- ratio of 3:1), did not adversely affect fertility or early embryonic development in the rat at doses of up to 20 mg/kg/day (approximately 8 times the maximum recommended human dose for adolescents of 20 mg/day, on a mg/m^2 body surface area basis).

13.2 Animal Toxicology and/or Pharmacology

Acute administration of high doses of amphetamine (d- or d,l-) has been shown to produce long-lasting neurotoxic effects, including irreversible nerve fiber damage, in rodents. The significance of these findings to humans is unknown.

14 CLINICAL STUDIES

Pediatric Patients

A double-blind, randomized, placebo-controlled, parallel-group study was conducted in children aged 6-12 (N=584) who met DSM-IV® criteria for ADHD (either the combined type or the hyperactive-impulsive type). Patients were randomized to fixed-dose treatment groups receiving final doses of 10, 20, or 30 mg of ADDERALL XR or placebo once daily in the morning for three weeks. Significant improvements in patient behavior, based upon teacher ratings of attention and hyperactivity, were observed for all ADDERALL XR doses compared to patients who received placebo, for all three weeks, including the first week of treatment, when all ADDERALL XR subjects were receiving a dose of 10 mg/day. Patients who received ADDERALL XR showed behavioral improvements in both morning and afternoon assessments compared to patients on placebo.

In a classroom analogue study, patients (N=51) receiving fixed doses of 10 mg, 20 mg or 30 mg ADDERALL XR demonstrated statistically significant improvements in teacher-rated behavior and performance measures, compared to patients treated with placebo.

A double-blind, randomized, multi-center, parallel-group, placebo-controlled study was conducted in adolescents aged 13-17 (N=327) who met DSM-IV® criteria for ADHD. The primary cohort of patients (n=287, weighing ≤ 75kg/165lbs) was randomized to fixed-dose treatment groups and received four weeks of treatment. Patients were randomized to receive final doses of 10 mg, 20 mg, 30 mg, and 40 mg ADDERALL XR or placebo once daily in the morning. Patients randomized to doses greater than 10 mg were titrated to their final doses by 10 mg each week. The secondary cohort consisted of 40 subjects weighing >75kg/165lbs who were randomized to fixed-dose treatment groups receiving final doses of 50 mg and 60 mg ADDERALL XR or placebo once daily in the morning for 4 weeks. The primary efficacy variable was the Attention Deficit Hyperactivity Disorder-Rating Scale IV (ADHD-RS-IV) total score for the primary cohort. The ADHD-RS-IV is an 18-item scale that measures the core symptoms of ADHD. Improvements in the primary cohort were statistically significantly greater in all four primary cohort active treatment groups (ADDERALL XR 10 mg, 20 mg, 30 mg, and 40 mg) compared with the placebo group. There was not adequate evidence that doses greater than 20 mg/day conferred additional benefit.

Adult Patients

A double-blind, randomized, placebo-controlled, parallel-group study was conducted in adults (N=255) who met DSM-IV® criteria for ADHD. Patients were randomized to fixed-dose treatment groups receiving final doses of 20, 40, or 60 mg of ADDERALL XR or placebo once daily in the morning for four weeks. Significant improvements, measured with the Attention Deficit Hyperactivity Disorder-Rating Scale (ADHD-RS), an 18- item scale that measures the core symptoms of ADHD, were observed at endpoint for all ADDERALL XR doses compared to patients who received placebo for all four weeks. There was not adequate evidence that doses greater than 20 mg/day conferred additional benefit.

16 HOW SUPPLIED/STORAGE AND HANDLING

ADDERALL XR 10 mg capsules: Blue/blue (imprinted ADDERALL XR 10 mg),

Bottles of 10 | NDC 54868-4760-3
Bottles of 20 | NDC 54868-4760-1
Bottles of 30 | NDC 54868-4760-2

ADDERALL XR 15 mg capsules: Blue/white (imprinted ADDERALL XR 15 mg),

Bottles of 10 | NDC 54868-5140-1
Bottles of 30 | NDC 54868-5140-0

ADDERALL XR 20 mg capsules: Orange/orange (imprinted ADDERALL XR 20 mg),

Bottles of 10 | NDC 54868-4640-1
Bottles of 30 | NDC 54868-4640-0
Bottles of 60 | NDC 54868-4640-2

ADDERALL XR 25 mg capsules: Orange/white (imprinted ADDERALL XR 25 mg),

Bottles of 10 | NDC 54868-5368-1
Bottles of 30 | NDC 54868-5368-0

ADDERALL XR 30 mg capsules: Natural/orange (imprinted ADDERALL XR 30 mg),

Bottles of 10 | NDC 54868-5142-1
Bottles of 30 | NDC 54868-5142-0

Dispense in a tight, light-resistant container as defined in the USP.

Store at 25° C (77° F). Excursions permitted to 15-30° C (59-86° F) [see USP Controlled Room Temperature]

17 PATIENT COUNSELING INFORMATION

17.1 Information on Medication Guide

Inform patients, their families, and their caregivers about the benefits and risks associated with treatment with ADDERALL XR and should counsel them in its appropriate use. A patient Medication Guide is available for ADDERALL XR. Instruct patients, their families, and their caregivers to read the Medication Guide and assist them in understanding its contents. Give patients the opportunity to discuss the contents of the Medication Guide and to obtain answers to any questions they may have. The complete text of the Medication Guide is reprinted at the end of this document.

17.2 Controlled Substance Status/Potential for Abuse, Misuse, and Dependence

Advise patients that ADDERALL XR is a federally controlled substance because it can be abused or lead to dependence. Additionally, emphasize that ADDERALL XR should be stored in a safe place to prevent misuse and/or abuse. Evaluate patient history (including family history) of abuse or dependence on alcohol, prescription medicines, or illicit drugs [see DRUG ABUSE AND DEPENDENCE (9)].

17.3 Serious Cardiovascular Risks

Advise patients of serious cardiovascular risk (including sudden death, myocardial infarction, stroke, and hypertension) with ADDERALL XR. Patients who develop symptoms such as exertional chest pain, unexplained syncope, or other symptoms suggestive of cardiac disease during treatment should undergo a prompt cardiac evaluation [see WARNINGS AND PRECAUTIONS (5.1)].

17.4 Psychiatric Risks

Prior to initiating treatment with ADDERALL XR, adequately screen patients with comorbid depressive symptoms to determine if they are at risk for bipolar disorder. Such screening should include a detailed psychiatric history, including a family history of suicide, bipolar disorder, and/or depression. Additionally, ADDERALL XR therapy at usual doses may cause treatment-emergent psychotic or manic symptoms in patients without prior history of psychotic symptoms or mania [see WARNINGS AND PRECAUTIONS (5.2)].

17.5 Growth

Monitor growth in children during treatment with ADDERALL XR, and patients who are not growing or gaining weight as expected may need to have their treatment interrupted [see WARNINGS AND PRECAUTIONS (5.3)].

17.6 Pregnancy

Advise patients to notify their physicians if they become pregnant or intend to become pregnant during treatment [see USE IN SPECIFIC POPULATIONS (8.1)].

17.7 Nursing

Advise patients not to breast feed if they are taking ADDERALL XR [see USE IN SPECIFIC POPULATIONS (8.3)].

17.8 Impairment in Ability to Operate Machinery or Vehicles

ADDERALL XR may impair the ability of the patient to engage in potentially hazardous activities such as operating machinery or vehicles; the patient should therefore be cautioned accordingly.

Manufactured for Shire US Inc., Wayne, PA 19087. Made in USA.

For more information call 1-800-828-2088

Pharmacist: Medication Guide to be dispensed to patients

ADDERALL XR® is registered in the US Patent and Trademark Office

ADDERALL® is a registered trademark of Shire LLC, under license to Duramed Pharmaceuticals, Inc.

Copyright© 2011, Shire US Inc.

Rev. 08/2011

Distributed and Repackaged by:
Physicians Total Care, Inc.
Tulsa, Oklahoma 74146

MEDICATION GUIDE

Read the Medication Guide that comes with ADDERALL XR before you or your child starts taking it and each time you get a refill. There may be new information. This Medication Guide does not take the place of talking to your doctor about you or your child's treatment with ADDERALL XR.

What is the most important information I should know about ADDERALL XR?
ADDERALL XR is a stimulant medicine. The following have been reported with use of stimulant medicines.
1. Heart-related problems:
• sudden death in patients who have heart problems or heart defects
• stroke and heart attack in adults
• increased blood pressure and heart rate
Tell your doctor if you or your child have any heart problems, heart defects, high blood pressure, or a family history of these problems.
Your doctor should check you or your child carefully for heart problems before starting ADDERALL XR.
Your doctor should check you or your child's blood pressure and heart rate regularly during treatment with ADDERALL XR.
Call your doctor right away if you or your child has any signs of heart problems such as chest pain, shortness of breath, or fainting while taking ADDERALL XR.
2. Mental (Psychiatric) problems:
All Patients
• new or worse behavior and thought problems
• new or worse bipolar illness
• new or worse aggressive behavior or hostility
Children and Teenagers
• new psychotic symptoms (such as hearing voices, believing things that are not true, are suspicious) or new manic symptoms
Tell your doctor about any mental problems you or your child have, or about a family history of suicide, bipolar illness, or depression.
Call your doctor right away if you or your child have any new or worsening mental symptoms or problems while taking ADDERALL XR, especially seeing or hearing things that are not real, believing things that are not real, or are suspicious.

What Is ADDERALL XR?

ADDERALL XR is a once daily central nervous system stimulant prescription medicine. It is used for the treatment of Attention Deficit Hyperactivity Disorder(ADHD). ADDERALL XR may help increase attention and decrease impulsiveness and hyperactivity in patients with ADHD.

ADDERALL XR should be used as a part of a total treatment program for ADHD that may include counseling or other therapies.

ADDERALL XR is a federally controlled substance (CII) because it can be abused or lead to dependence. Keep ADDERALL XR in a safe place to prevent misuse and abuse. Selling or giving away ADDERALL XR may harm others, and is against the law.
Tell your doctor if you or your child have (or have a family history of) ever abused or been dependent on alcohol, prescription medicines or street drugs.

Who should not take ADDERALL XR?

ADDERALL XR should not be taken if you or your child:

- have heart disease or hardening of the arteries
- have moderate to severe high blood pressure
- have hyperthyroidism
- have an eye problem called glaucoma
- are very anxious, tense, or agitated
- have a history of drug abuse
- are taking or have taken within the past 14 days an anti-depression medicine called a monoamine oxidase inhibitor or MAOI.
- is sensitive to, allergic to, or had a reaction to other stimulant medicines

ADDERALL XR has not been studied in children less than 6 years old.

ADDERALL XR may not be right for you or your child. Before starting ADDERALL XR tell your or your child's doctor about all health conditions (or a family history of) including:

- heart problems, heart defects, or high blood pressure
- mental problems including psychosis, mania, bipolar illness, or depression
- tics or Tourette's syndrome
- liver or kidney problems
- thyroid problems
- seizures or have had an abnormal brain wave test (EEG)

Tell your doctor if you or your child is pregnant, planning to become pregnant, or breastfeeding.

Can ADDERALL XR be taken with other medicines?

Tell your doctor about all of the medicines that you or your child takes including prescription and non-prescription medicines, vitamins, and herbal supplements. ADDERALL XR and some medicines may interact with each other and cause serious side effects. Sometimes the doses of other medicines will need to be adjusted while taking ADDERALL XR.

Your doctor will decide whether ADDERALL XR can be taken with other medicines.

Especially tell your doctor if you or your child takes:

- anti-depression medicines including MAOIs
- anti-psychotic medicines
- lithium
- narcotic pain medicines
- seizure medicines
- blood thinner medicines
- blood pressure medicines
- stomach acid medicines
- cold or allergy medicines that contain decongestants

Know the medicines that you or your child takes. Keep a list of your medicines with you to show your doctor and pharmacist.

Do not start any new medicine while taking ADDERALL XR without talking to your doctor first.

How should ADDERALL XR be taken?

- Take ADDERALL XR exactly as prescribed. Your doctor may adjust the dose until it is right for you or your child.
- Take ADDERALL XR once a day in the morning when you first wake up. ADDERALL XR is an extended release capsule. It releases medicine into your body throughout the day.
- Swallow ADDERALL XR capsules whole with water or other liquids. If you or your child cannot swallow the capsule, open it and sprinkle the medicine over a spoonful of applesauce. Swallow all of the applesauce and medicine mixture without chewing immediately. Follow with a drink of water or other liquid. Never chew or crush the capsule or the medicine inside the capsule.
- ADDERALL XR can be taken with or without food.
- From time to time, your doctor may stop ADDERALL XR treatment for a while to check ADHD symptoms.
- Your doctor may do regular checks of the blood, heart, and blood pressure while taking ADDERALL XR. Children should have their height and weight checked often while taking ADDERALL XR. ADDERALL XR treatment may be stopped if a problem is found during these check-ups.
- If you or your child takes too much ADDERALL XR or overdoses, call your doctor or poison control center right away, or get emergency treatment.

What are possible side effects of ADDERALL XR?

See "What is the most important information I should know about ADDERALL XR?" for information on reported heart and mental problems.

Other serious side effects include:

- slowing of growth (height and weight) in children
- seizures, mainly in patients with a history of seizures
- eyesight changes or blurred vision

Common side effects include:

- headache
- decreased appetite
- stomach ache
- nervousness
- trouble sleeping
- mood swings
- weight loss
- dizziness
- dry mouth
- fast heart beat

ADDERALL XR may affect you or your child's ability to drive or do other dangerous activities.

Talk to your doctor if you or your child has side effects that are bothersome or do not go away.

This is not a complete list of possible side effects. Ask your doctor or pharmacist for more information

Call your doctor for medical advice about side effects. You may report side effects to FDA at 1-800-FDA-1088.

How should I store ADDERALL XR?

- Store ADDERALL XR in a safe place at room temperature, 59 to 86° F (15 to 30° C).
- Keep ADDERALL XR and all medicines out of the reach of children.

General information about ADDERALL XR

Medicines are sometimes prescribed for purposes other than those listed in a Medication Guide. Do not use ADDERALL XR for a condition for which it was not prescribed. Do not give ADDERALL XR to other people, even if they have the same condition. It may harm them and it is against the law.

This Medication Guide summarizes the most important information about ADDERALL XR. If you would like more information, talk with your doctor. You can ask your doctor or pharmacist for information about ADDERALL XR that was written for healthcare professionals. For more information, you may also contact Shire Pharmaceuticals (the maker of ADDERALL XR) at 1-800-828-2088 or visit the website at http://www.adderallxr.com.

What are the ingredients in ADDERALL XR?

Active Ingredients: dextroamphetamine saccharate, amphetamine aspartate monohydrate, dextroamphetamine sulfate, USP, amphetamine sulfate USP

Inactive Ingredients: gelatin capsules, hydroxypropyl methylcellulose, methacrylic acid copolymer, opadry beige, sugar spheres, talc, and triethyl citrate. Gelatin capsules contain edible inks, kosher gelatin, and titanium dioxide. The 5 mg, 10 mg, and 15 mg capsules also contain FD&C Blue #2. The 20 mg, 25 mg, and 30 mg capsules also contain red iron oxide and yellow iron oxide

Manufactured for Shire US Inc., Wayne, PA 19087.

ADDERALL XR is registered in the US Patent and Trademark Office © 2011 Shire US Inc

Rev. 08/2011

This Medication Guide has been approved by the U.S. Food and Drug Administration.

PACKAGE LABEL

ADDERALL XR®

5 mg bottle

10 mg bottle

15 mg bottle

20 mg bottle

25 mg bottle

30 mg bottle